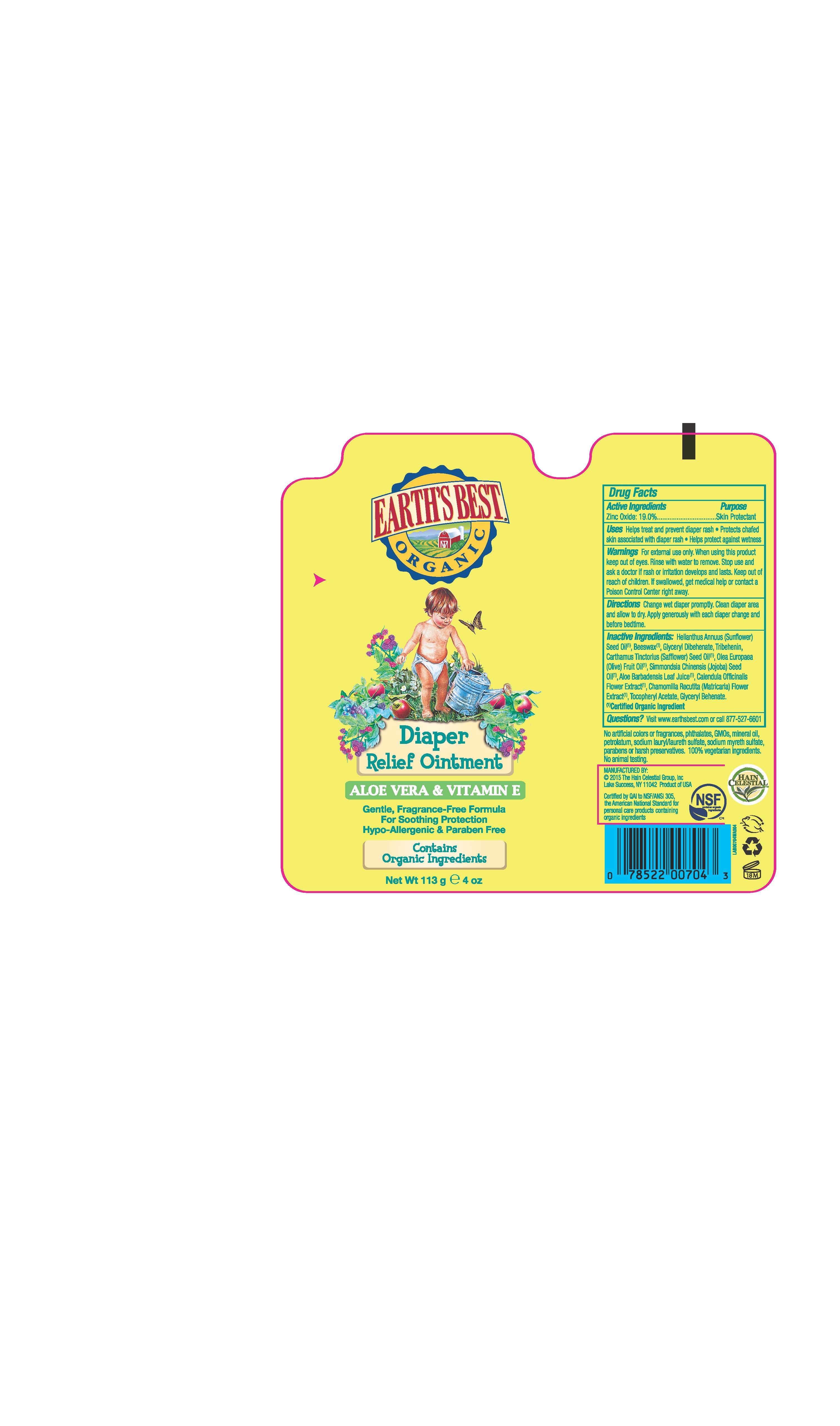 DRUG LABEL: Earth Best Diaper Relief
NDC: 61995-4704 | Form: OINTMENT
Manufacturer: The Hain Celestial Group, Inc
Category: otc | Type: HUMAN OTC DRUG LABEL
Date: 20210205

ACTIVE INGREDIENTS: ZINC OXIDE 19 g/100 g
INACTIVE INGREDIENTS: ALOE VERA LEAF; CHAMOMILE; ALPHA-TOCOPHEROL ACETATE; GLYCERYL MONOBEHENATE; GLYCERYL DIBEHENATE; SAFFLOWER OIL; OLIVE OIL; JOJOBA OIL; CALENDULA OFFICINALIS FLOWER; SUNFLOWER OIL; TRIBEHENIN; YELLOW WAX

Earth's Best Diaper Relief Ointment

ACTIVE INGREDIENT

Zinc Oxide 19.0%

PURPOSE

Skin Protectant

INDICATIONS AND USAGE

- Helps treat and prevent diaper rash.
- Protects chafed skin associated with diaper rash.
- Helps protect against wetness

WARNINGS

For external use only. When using this product keep out of eyes. Rinse with water to remove. Stop use and ask doctor if rash or irritation develops and lasts.

Keep out of reach of children. If swallowed get medical help or contact Poison Center right away.

DOSAGE AND ADMINISTRATION

Change wet diaper promptly. Clean diaper area and allow to dry. Apply generously with each diaper change and before bedtime.

INACTIVE INGREDIENT

Helianthus Annuus (Sunflower) Seed Oil * ,Beeswax*, Glyceryl Dibehenate, Tribehenin, Carthamus Tinctorius (Safflower) Oil* , Olea Europea (Olive) Fruit Oil *, Simmondsia Chinensis (Jojoba) Seed Oil*, Aloe Barbadensis Leaf Juice* , Calendula Officinalis Flower Extract* , Chamomilla Recutita (Matricaria) Flower Extract *, Glycerin *, Glyceryl Behenate, Tocopheryl Acetate.

* Certified Organic Ingredients

QUESTIONS

Questions? Visit www.earthsbest.com or cal l877-527-6601